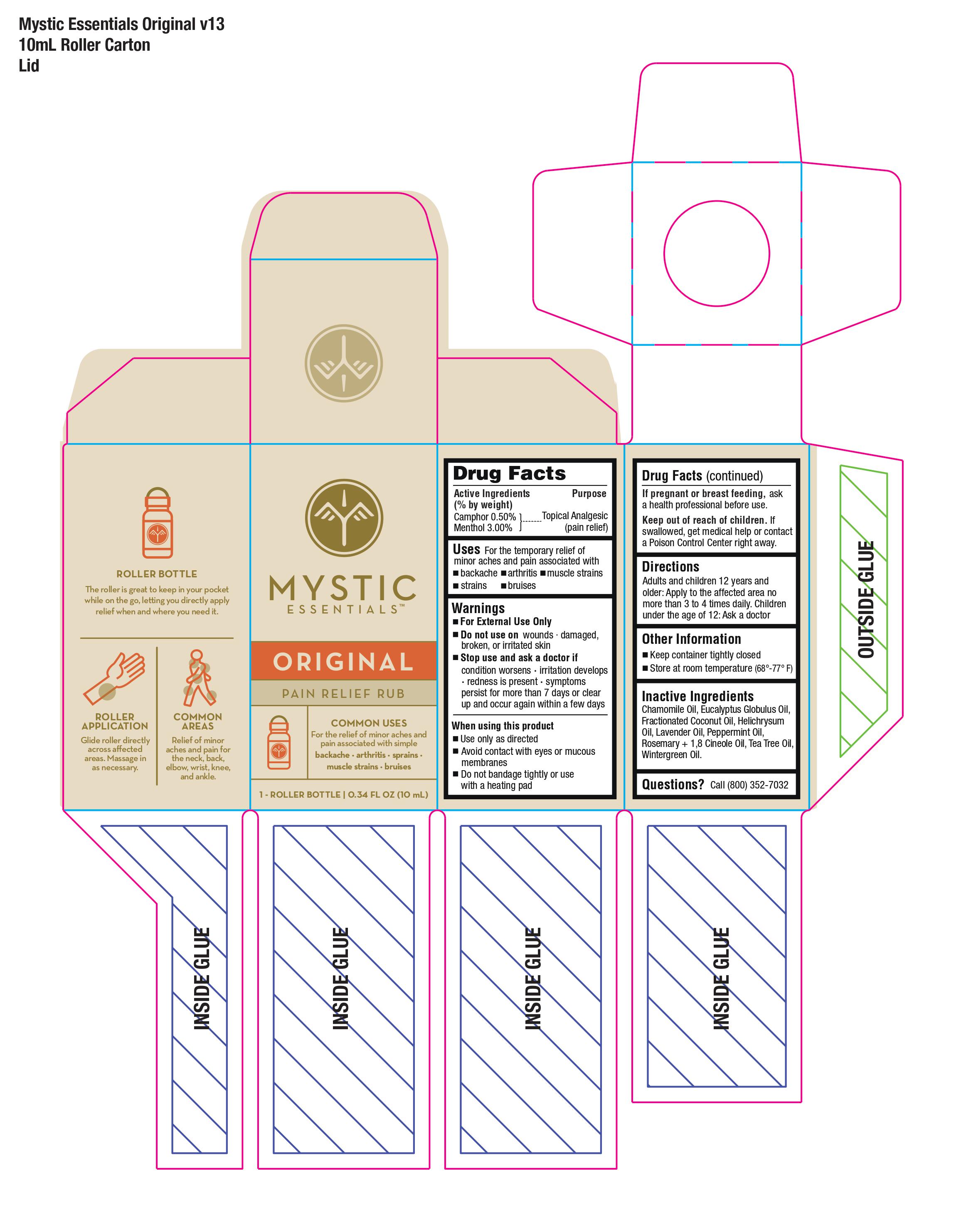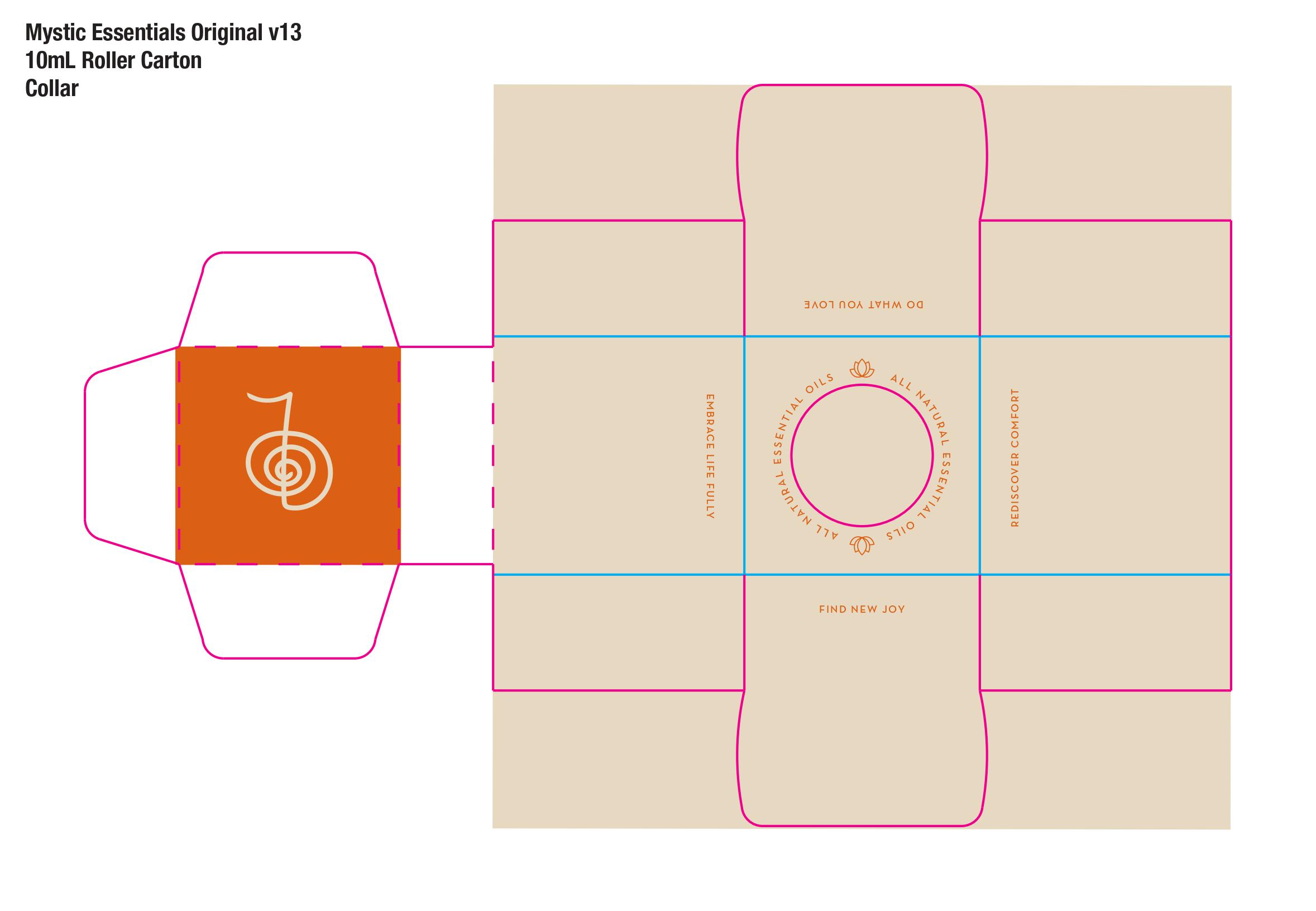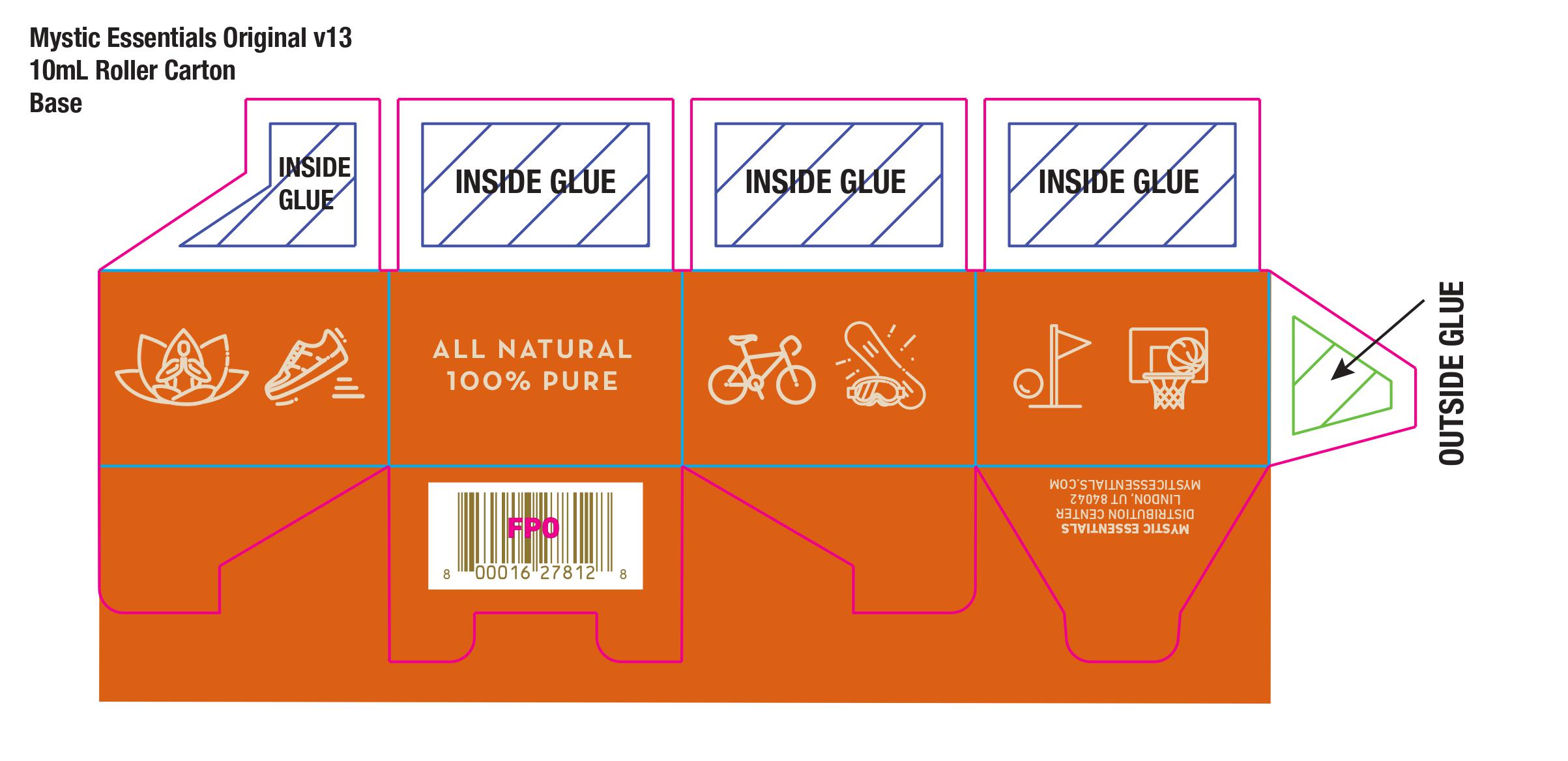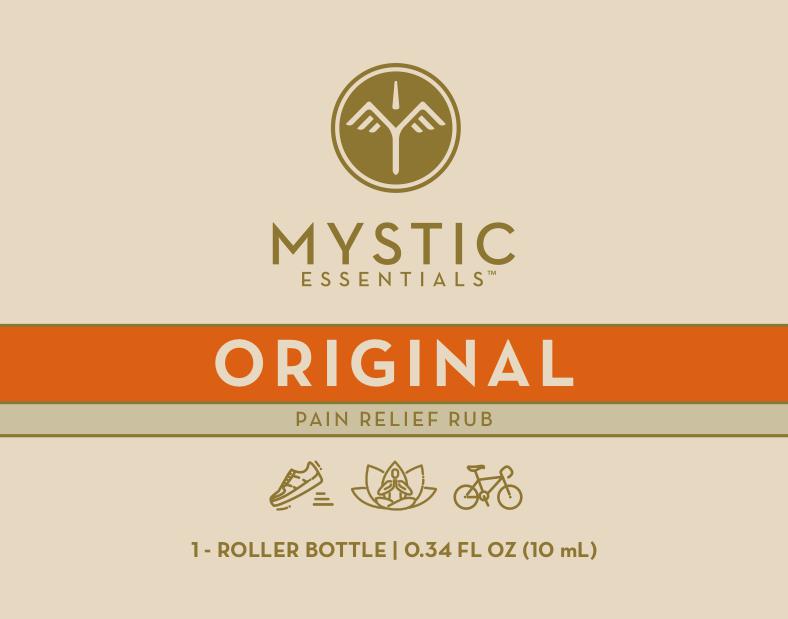 DRUG LABEL: Mystic Essentials Original Pain Relief Rub
NDC: 73769-450 | Form: LIQUID
Manufacturer: NATURE'S FUSIONS, LLC
Category: otc | Type: HUMAN OTC DRUG LABEL
Date: 20240801

ACTIVE INGREDIENTS: CAMPHOR (NATURAL) 0.5 g/100 g; MENTHOL 3 g/100 g
INACTIVE INGREDIENTS: ROSEMARY OIL; CHAMOMILE FLOWER OIL; LAVENDER OIL; METHYL SALICYLATE; MEDIUM-CHAIN TRIGLYCERIDES; PEPPERMINT OIL; EUCALYPTUS OIL; HELICHRYSUM ITALICUM FLOWER OIL; TEA TREE OIL

USES

For the temporary relief of minor aches and pain associated with *backache *arthritis *muscle strains *strains *bruises

ACTIVE INGREDIENT

Camphor 0.5% - Topical Analgesic (pain relief)

Menthol 3.00% - Topical Analgesic (pain relief)

WARNINGS

- For External Use Only
- Do not use on wounds - damaged, broken, or irritated skin
- Stop use and ask doctor if condition worsens * irritation develops *redness is present *symptoms persist for more than 7 days or clear up and occur again within a few days

______________________________

When using this product

- Use only as directed
- Avoid contact with eyes or mucous membranes
- Do not bandage tightly or use with a heating pad.
- ______________________________

If Pregnant or breast feeding, ask a health professional before use.

Directions

Adults and children 12 years and older: Apply to the affected area no more than 3 to 4 times daily. Children under the age of 12: Ask a doctor.

Other Information

- Keep container tightly closed
- Store at room temperature (68°-77° F)

Inactive Ingredients

Chamomile Oil, Eucalyptus Globulus Oil, Fractionated Coconut Oil, Helichrysum Oil, Lavender Oil, Peppermint Oil, Rosemary + 1,8 Cineole Oil, Tea Tree Oil, Wintergreen Oil.

OTHER SAFETY INFORMATION

Questions? Call (800) 352-7032

KEEP OUT OF REACH OF CHILDREN

Keep our of reach of children. If swallowed, get medical help or contact a Poison Control Center right away.

Directions

Adults and children 12 years and older: Apply to the affected area no more than 3 to 4 times daily. Children under the age of 12: Ask a doctor.

PACKAGE LABEL

0.34 FL OZ (10ml) Carton Display Panel